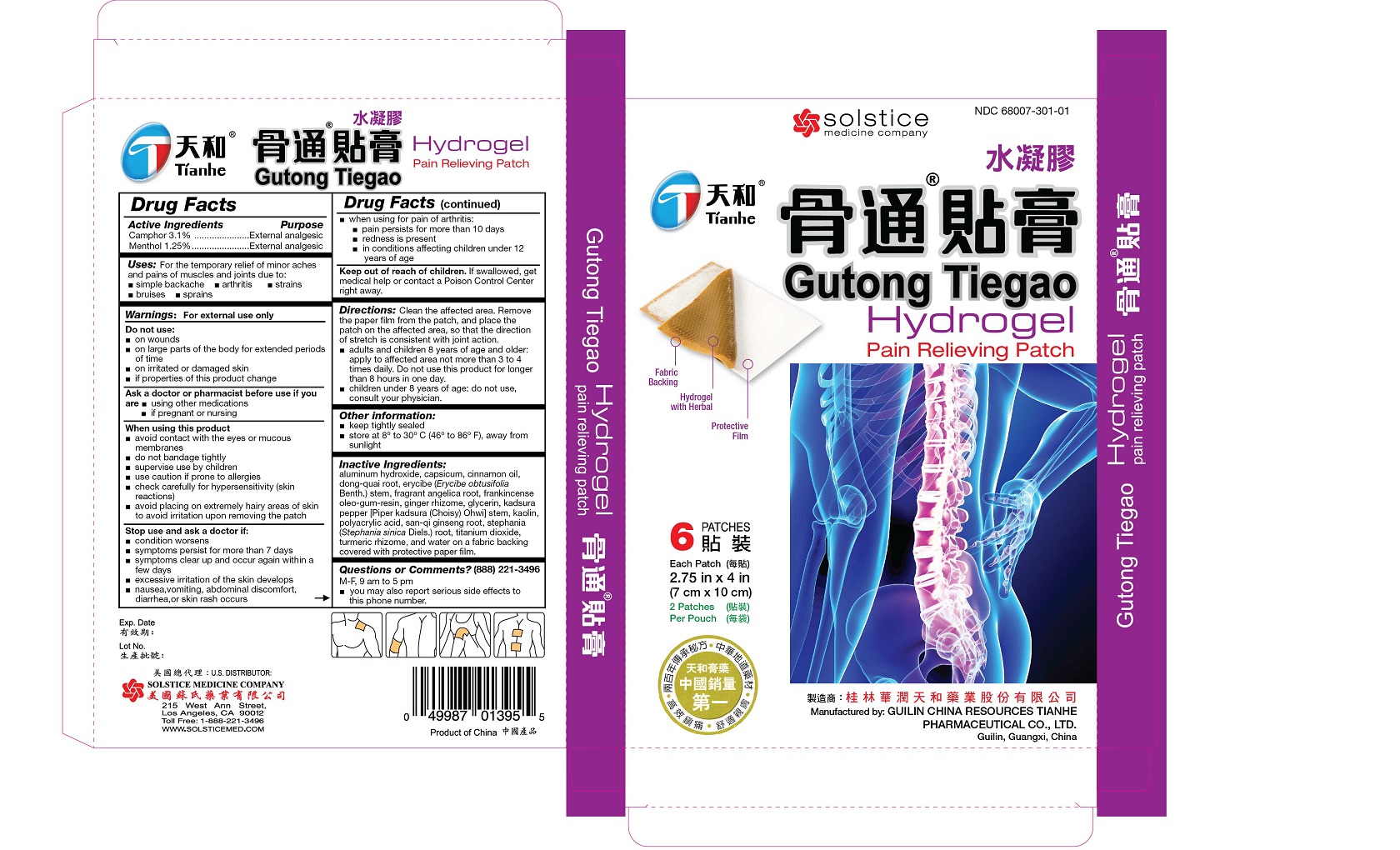 DRUG LABEL: GUTONG TIEGAO PAIN RELIEVING
NDC: 68007-301 | Form: PATCH
Manufacturer: GUILIN CHINA RESOURCES TIANHE PHARMACEUTICAL CO LTD
Category: otc | Type: HUMAN OTC DRUG LABEL
Date: 20250926

ACTIVE INGREDIENTS: CAMPHOR (SYNTHETIC) 248 mg/1 1; MENTHOL 100 mg/1 1
INACTIVE INGREDIENTS: ALUMINUM HYDROXIDE; CAPSICUM; CINNAMON OIL; ANGELICA SINENSIS ROOT; ERYCIBE OBTUSIFOLIA STEM; ANGELICA DAHURICA ROOT; FRANKINCENSE; ZINGIBER OFFICINALE WHOLE; GLYCERIN; PIPER KADSURA STEM; KAOLIN; POLYACRYLIC ACID (800000 MW); PANAX NOTOGINSENG ROOT; HUPERZIA SERRATA; TITANIUM DIOXIDE; TURMERIC; WATER

DRUG FACTS

Active ingredients

Camphor 3.1%

Menthol 1.25%

Purpose

External analgesic

Uses

For the temporary relief of minor aches and pains of muscles and joints due to:

simple backache

arthritis

strains

bruises

sprains

Warnings

For external use only

Do not use

on wounds

on large parts of the body for extended periods of time

on irritated or damaged skin

if properties of this product change

Ask a doctor or pharmacist before use if you are

using other medications

if pregnant or nursing

When using this product

avoid contact with the eyes or mucous membranes

do not bandage tightly

supervise use by children

use caution if prone to allergies

check carefully for hypersensitivity (skin reactions)

avoid placing on extremely hairy areas of skin to avoid irritation upon removing the patch

Stop use and ask a doctor if

condition worsens

symptoms persist for more than 7 days

symptoms clear up and occur again within a few days

excessive irritation of the skin develops

nausea, vomiting, abdominal discomfort, diarrhea, or skin rash occurs

when using for pain of arthritis:

pain persists for more than 10 days

redness is present

in conditions affecting children under 12 years of age

Keep out of reach of children.If swallowed, get medical help or contact a Poison Control Center right away.

Directions

Clean the affected area. Remove the paper film from the patch, and place the patch on the affected area, so that the direction of stretch is consistent with joint action.

adults and children 8 years of age and older: apply to affected area not more than 3 to 4 times daily. Do not use this product for longer than 8 hours in one day.

children under 8 years of age: do not use, consult your physician

Other information

keep tightly sealed

store at 8 to 30 C (46 to 86 F), away from sunlight

Inactive ingredients

aluminum hydroxide, capsicum, cinnamon oil, dong-quai root, erycibe (Erycibe obtusifolia Benth.) stem, fragrant angelica root, frankincense oleo-gum-resin, ginger rhizome, glycerin, kadsura pepper [Piper kadsura (Choisy) Ohwi] stem, kaolin, polyacrylic acid, san-qi ginseng root, stephania (Stephania sinica Diels.) root, titanium dioxide, turmeric rhizome, and water on a fabric backing covered with protective paper film.

Questions or comments?(888) 221-3496 M-F 9 am to 5 pm

you may also report serious side effects to this phone number

PACKAGE LABEL

Gutong Tiegao Hydrogel Pain Relieving Patch

NDC 68007-301-01

6 Patches

Each Patch 2.75 in x 4 in (7 cm x 10 cm)

2 Patches Per Pouch